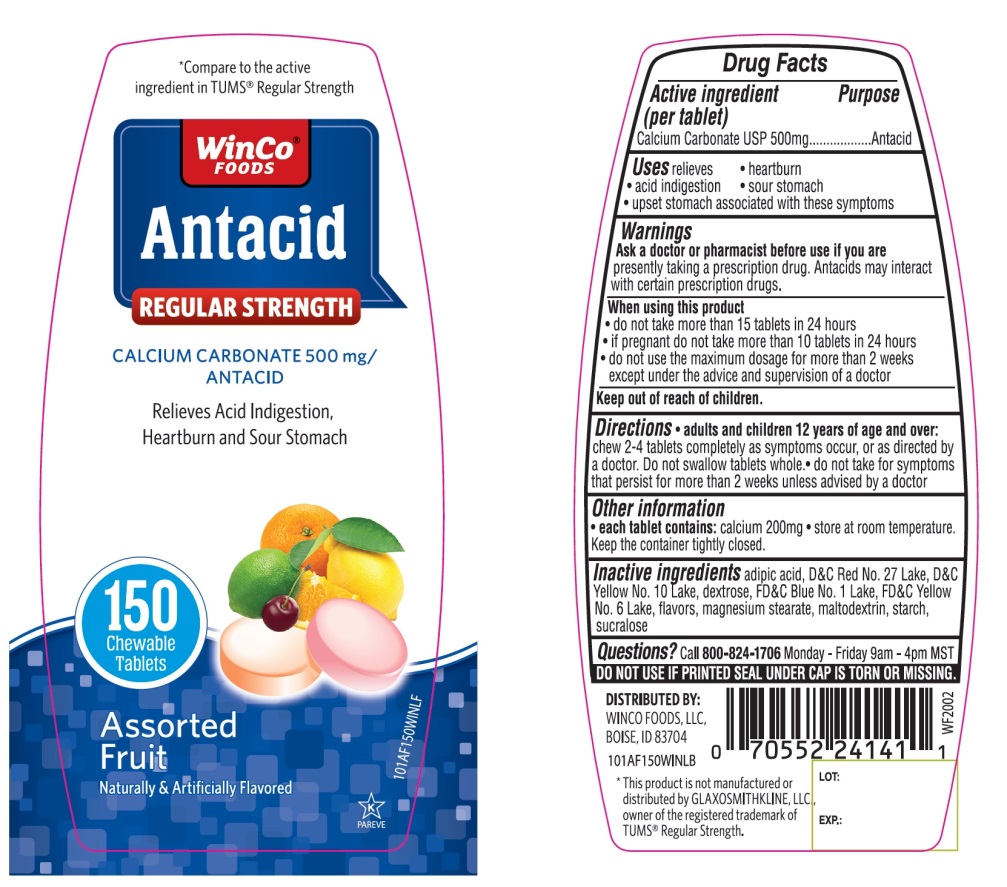 DRUG LABEL: WinCo FOODS Antacid

NDC: 67091-356 | Form: TABLET, CHEWABLE
Manufacturer: WINCO FOODS, LLC
Category: otc | Type: HUMAN OTC DRUG LABEL
Date: 20251202

ACTIVE INGREDIENTS: CALCIUM CARBONATE 500 mg/1 1
INACTIVE INGREDIENTS: ADIPIC ACID; D&C RED NO. 27; D&C YELLOW NO. 10; DEXTROSE, UNSPECIFIED FORM; FD&C BLUE NO. 1; FD&C YELLOW NO. 6; MAGNESIUM STEARATE; MALTODEXTRIN; STARCH, CORN; SUCRALOSE

WinCo®FOODS Regular Strength Assorted Fruits Chewable Tablets

Active ingredient (per tablet)

Calcium Carbonate USP 500mg

Purpose

Antacid

Uses

relieves

• heartburn

• acid indigestion

• sour stomach

• upset stomach associated with these symptoms

Warnings

Ask a doctor or pharmacist before use if you arepresently taking a prescription drug. Antacids may interact with certain prescription drugs.

When using this product

- do not take more than 15 tablets in 24 hours
- If pregnant do not take more than10 tablets in 24 hours
- do not use the maximum dosage for more than 2 weeks except under the advice and supervision of a doctor.

Directions

- adults and children 12 years of age and over: chew 2-4 tablets completely as symptoms occur, or as directed by a doctor. Do not swallow tablets whole.
- do not take for symptoms that persist for more than 2 weeks unless advised by a doctor.

Other information

• each tablet contains:calcium 200 mg

• store at room temperature. Keep the container tightly closed

Inactive ingredients

adipic acid, D&C Red No. 27 Lake, D&C Yellow No. 10 Lake, dextrose, FD&C Blue No. 1 Lake, FD&C Yellow No. 6, flavors, magnesium stearate, maltodextrin, starch, sucralose

Questions or comments?

Call 1-800-824-1706

SAFETY SEALED: DO NOT USE IF PRINTED SEAL UNDER CAP IS TORN OR MISSING.

Package/Label Principal Display Panel

WinCo® FOODS

Compare to active ingredient in TUMS®Regular Strength

Antacid

REGULAR STRENGTH

CALCIUM CARBONATE 500 mg/ANTACID

Relieves Acid Indigestion, Heartburn and Sour Stomach

150 Chewable Tablets

Assorted Fruit

Naturally & Artificially Flavored

GLUTEN-FREE

DISTRIBUTED BY: WINCO FOODS, LLC.

BOISE, ID 837047

*This product is not manufactured or distributed by GLAXOSMITHKLINE, LLC owner of the registered trademark of TUMS®Regular Strength.